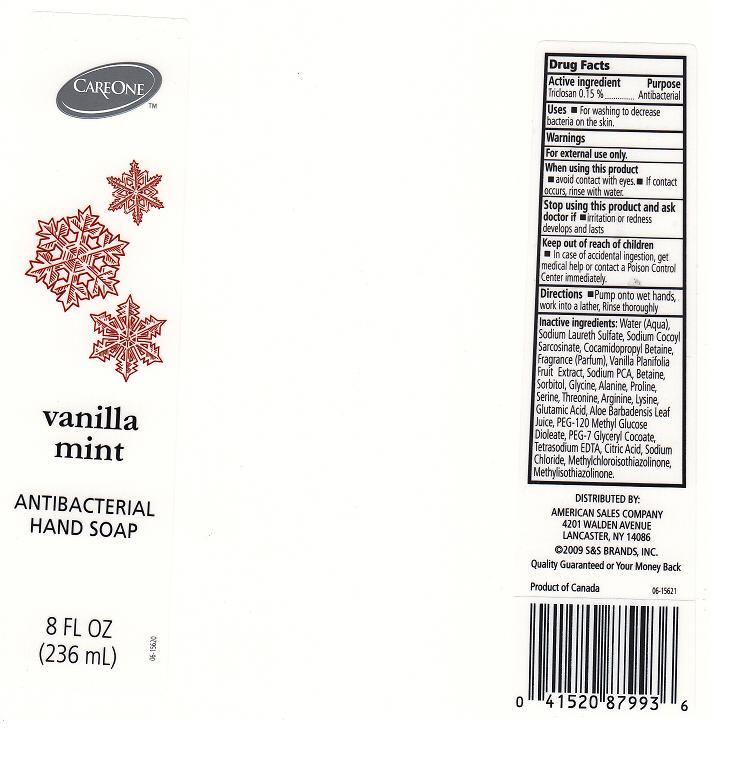 DRUG LABEL: ANTIBACTERIAL
NDC: 41520-283 | Form: LIQUID
Manufacturer: AMERICAN SALES COMPANY
Category: otc | Type: HUMAN OTC DRUG LABEL
Date: 20110622

ACTIVE INGREDIENTS: TRICLOSAN 0.15 mL/100 mL
INACTIVE INGREDIENTS: WATER; SODIUM LAURETH SULFATE; COCAMIDOPROPYL BETAINE; VANILLA; SODIUM PYRROLIDONE CARBOXYLATE; BETAINE; SORBITOL; GLYCINE; ALANINE; PROLINE; SERINE; THREONINE; ARGININE; LYSINE; GLUTAMIC ACID; ALOE VERA LEAF; PEG-120 METHYL GLUCOSE DIOLEATE; PEG-7 GLYCERYL COCOATE; EDETATE SODIUM; CITRIC ACID MONOHYDRATE; SODIUM CHLORIDE; METHYLCHLOROISOTHIAZOLINONE; METHYLISOTHIAZOLINONE

DRUG FACTS

ACTIVE INGREDIENT

TRICLOSAN 0.15%

PURPOSE

ANTIBACTERIAL

USES

FOR WASHING TO DECREASE BACTERIA ON THE SKIN.

WARNINGS

FOR EXTERNAL USE ONLY.

WHEN USING THIS PRODUCT

AVOID CONTACT WITH EYES. IF CONTACT OCCURS, RINSE WITH WATER.

STOP USING THIS PRODUCT AND ASK DOCTOR IF

IRRITATION OR REDNESS DEVELOPS AND LASTS.

KEEP OUT OF REACH OF CHILDREN

IN CASE OF ACCIDENTAL INGESTION, GET MEDICAL HELP OR CONTACT A POISON CONTROL CENTER IMMEDIATELY.

DIRECTIONS

PUMP ONTO WET HANDS, WORK INTO A LATHER, RINSE THROUGHLY.

INACTIVE INGREDIENT

WATER, SODIUM LAURETH SULFATE, SODIUM COCOYL SARCOSINATE, COCAMIDOPROPYL BETAINE, FRAGRANCE, VANILLA PLANIFOLIA FRUIT EXTRACT, SODIUM PCA, BETAINE, SORBITOL, GLYCINE, ALANINE, PROLINE, SERINE, THREONINE, ARGININE, LYSINE, GLUTAMIC ACID, ALOE BARBADENSIS LEAF JUICE, PEG-120 METHYL GLUCOSE DIOLEATE, PEG-7 GLYCERYL COCOATE, TETRASODIUM EDTA, CITRIC ACID, SODIUM CHLORIDE, METHYLCHLOROISOTHIAZOLINONE, METHYLISOTHIAZOLINONE.